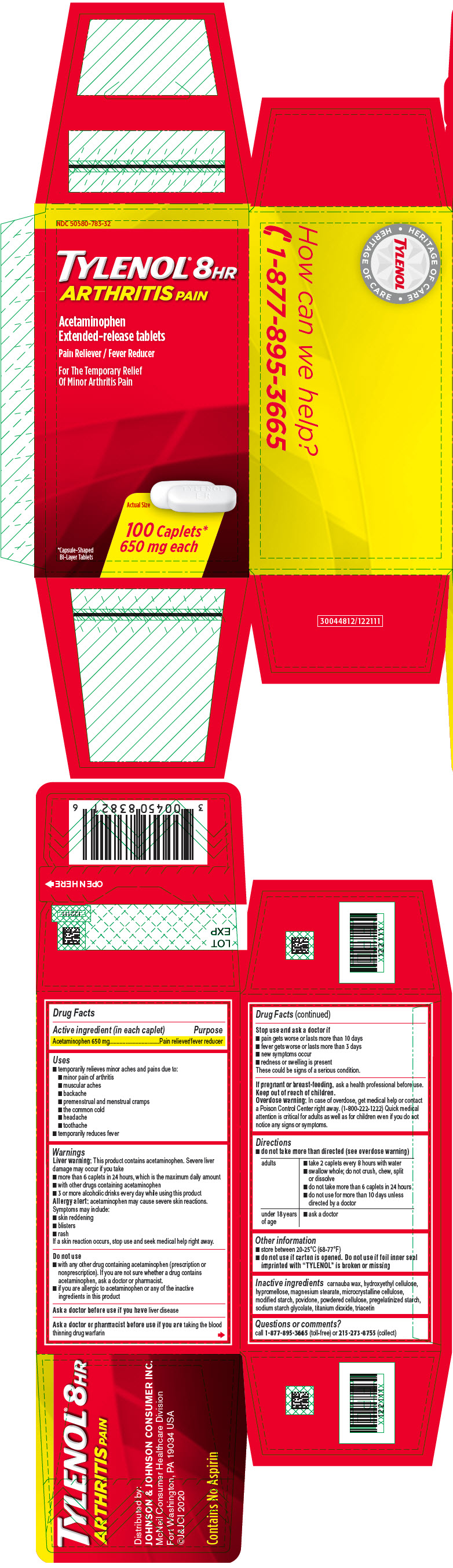 DRUG LABEL: Tylenol 8 HR Arthritis Pain
NDC: 50580-783 | Form: TABLET, EXTENDED RELEASE
Manufacturer: Kenvue Brands LLC
Category: otc | Type: HUMAN OTC DRUG LABEL
Date: 20241113

ACTIVE INGREDIENTS: ACETAMINOPHEN 650 mg/1 1
INACTIVE INGREDIENTS: CARNAUBA WAX; HYDROXYETHYL CELLULOSE, UNSPECIFIED; HYPROMELLOSE, UNSPECIFIED; MAGNESIUM STEARATE; MICROCRYSTALLINE CELLULOSE; POVIDONE, UNSPECIFIED; POWDERED CELLULOSE; SODIUM STARCH GLYCOLATE TYPE A; TITANIUM DIOXIDE; TRIACETIN

Tylenol® 8 HR Arthritis Pain

Drug Facts

Active ingredient (in each caplet)

Acetaminophen 650 mg

Purpose

Pain reliever/fever reducer

Uses

- temporarily relieves minor aches and pains due to:
  - minor pain of arthritis
  - muscular aches
  - backache
  - premenstrual and menstrual cramps
  - the common cold
  - headache
  - toothache
- temporarily reduces fever

Warnings

Liver warning

This product contains acetaminophen. Severe liver damage may occur if you take

- more than 6 caplets in 24 hours, which is the maximum daily amount
- with other drugs containing acetaminophen
- 3 or more alcoholic drinks every day while using this product

Allergy alert: acetaminophen may cause severe skin reactions. Symptoms may include:

- skin reddening
- blisters
- rash

If a skin reaction occurs, stop use and seek medical help right away.

Do not use

- with any other drug containing acetaminophen (prescription or nonprescription). If you are not sure whether a drug contains acetaminophen, ask a doctor or pharmacist.
- if you are allergic to acetaminophen or any of the inactive ingredients in this product

Ask a doctor before use if you have liver disease

Ask a doctor or pharmacist before use if you are taking the blood thinning drug warfarin

Stop use and ask a doctor if

- pain gets worse or lasts more than 10 days
- fever gets worse or lasts more than 3 days
- new symptoms occur
- redness or swelling is present

These could be signs of a serious condition.

PREGNANCY OR BREAST FEEDING

If pregnant or breast-feeding, ask a health professional before use.

Keep out of reach of children.

Overdose warning

In case of overdose, get medical help or contact a Poison Control Center right away. (1-800-222-1222) Quick medical attention is critical for adults as well as for children even if you do not notice any signs or symptoms.

Directions

- do not take more than directed (see overdose warning)

adults | - take 2 caplets every 8 hours with water - swallow whole; do not crush, chew, split or dissolve - do not take more than 6 caplets in 24 hours - do not use for more than 10 days unless directed by a doctor
under 18 years of age | - ask a doctor

Other information

- store between 20-25°C (68-77°F)
- do not use if carton is opened. Do not use if foil inner seal imprinted with "TYLENOL" is broken or missing

Inactive ingredients

carnauba wax, hydroxyethyl cellulose, hypromellose, magnesium stearate, microcrystalline cellulose, modified starch, povidone, powdered cellulose, pregelatinized starch, sodium starch glycolate, titanium dioxide, triacetin

Questions or comments?

call 1-877-895-3665 (toll-free) or 215-273-8755 (collect)

PRINCIPAL DISPLAY PANEL

NDC 50580-783-32

TYLENOL® 8HR

ARTHRITIS PAIN

Acetaminophen
Extended-release tablets

Pain Reliever / Fever Reducer

For The Temporary Relief
Of Minor Arthritis Pain

*Capsule-Shaped
Bi-Layer Tablets

Actual Size

100 Caplets*
650 mg each